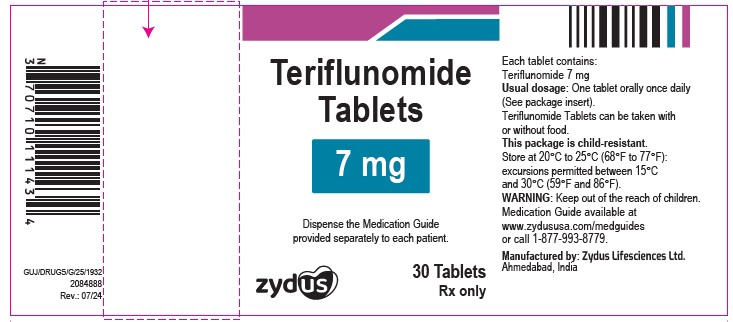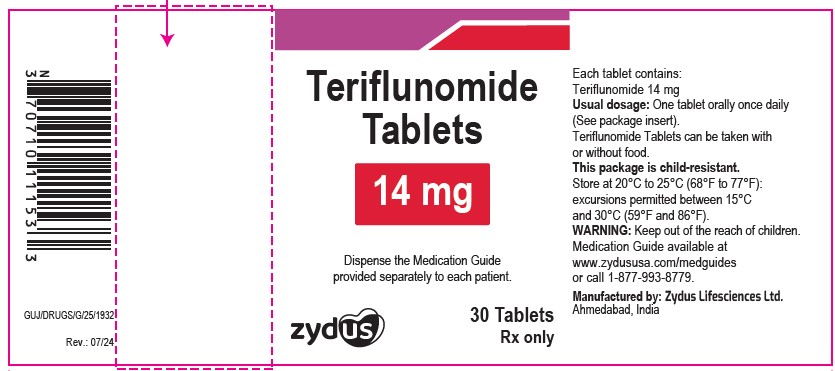 DRUG LABEL: Teriflunomide
NDC: 70771-1010 | Form: TABLET, FILM COATED
Manufacturer: Zydus Lifesciences Limited
Category: prescription | Type: HUMAN PRESCRIPTION DRUG LABEL
Date: 20240812

ACTIVE INGREDIENTS: TERIFLUNOMIDE 7 mg/1 1
INACTIVE INGREDIENTS: CELLULOSE, MICROCRYSTALLINE; HYPROMELLOSES; LACTOSE MONOHYDRATE; MAGNESIUM STEARATE; POLYETHYLENE GLYCOL, UNSPECIFIED; SODIUM STARCH GLYCOLATE TYPE A POTATO; STARCH, CORN; TITANIUM DIOXIDE

Teriflunomide Tablets

PACKAGE LABEL.PRINCIPAL DISPLAY PANEL

NDC 70771-1010-3

Teriflunomide Tablets, 7 mg

30 Tablets

Rx only

NDC 70771-1011-3

Teriflunomide Tablets, 14 mg

30 Tablets

Rx only